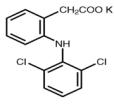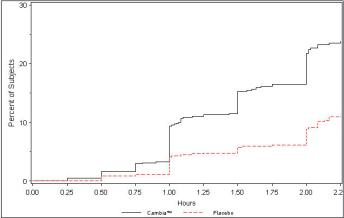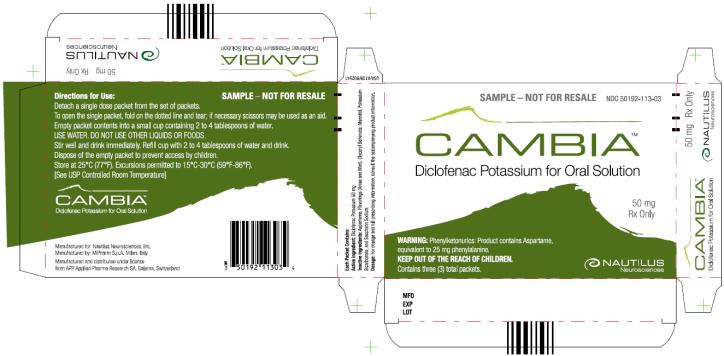 DRUG LABEL: CAMBIA
NDC: 50192-113 | Form: POWDER, FOR SOLUTION
Manufacturer: Nautilus Neurosciences, Inc.
Category: prescription | Type: HUMAN PRESCRIPTION DRUG LABEL
Date: 20120329

ACTIVE INGREDIENTS: DICLOFENAC POTASSIUM 1 mg/1 mg
INACTIVE INGREDIENTS: ASPARTAME; GLYCERYL BEHENATE; MANNITOL; POTASSIUM BICARBONATE; SACCHARIN SODIUM

HIGHLIGHTS OF PRESCRIBING INFORMATION

These highlights do not include all the information needed to use CAMBIA safely and effectively. See full prescribing information for CAMBIA.
CAMBIA (Diclofenac Potassium for Oral Solution)
Initial U.S. Approval: 1988

WARNING: RISK OF SERIOUS CARDIOVASCULAR AND GASTROINTESTINAL EVENTS

See full prescribing information for complete boxed warning

Cardiovascular Risk

- Non-steroidal anti-inflammatory drugs (NSAIDs) may increase the risk of serious cardiovascular (CV) thrombotic events, myocardial infarction, and stroke, which can be fatal. Risk may increase with duration of use. (5.1)
- CAMBIA is contraindicated for the treatment of peri-operative pain in the setting of coronary artery bypass graft (CABG) surgery. (4, 5.1)

Gastrointestinal Risk

- NSAIDs increase the risk of serious gastrointestinal (GI) adverse events including bleeding, ulceration, and perforation of the stomach or intestines, which can be fatal. Events can occur at any time without warning symptoms. Elderly patients are at greater risk. (5.2)

1 INDICATIONS AND USAGE

CAMBIA is a non-steroidal anti-inflammatory (NSAID) drug indicated for the acute treatment of migraine attacks with or without aura in adults 18 years of age or older (1.1)

Important Limitations (1.2):

- CAMBIA is not indicated for the prophylactic therapy of migraine
- Safety and effectiveness of CAMBIA not established for cluster headache, which is present in an older, predominantly male population

2 DOSAGE AND ADMINISTRATION

Single 50 mg dose; mix single packet contents with 1 to 2 ounces (30 to 60 mL) of water prior to administration (1)

3 DOSAGE FORMS AND STRENGTHS

Packets: Each containing buffered diclofenac potassium 50 mg in a soluble powder (3)

4 CONTRAINDICATIONS

- Known hypersensitivity to diclofenac or NSAIDs (4)
- Pre-existing asthma, urticaria, or allergic-type reactions after taking aspirin or other NSAIDs (4)
- Use during the peri-operative period in the setting of coronary artery bypass graft (CABG) surgery (4, 5.1)

5 WARNINGS AND PRECAUTIONS

- Serious and potentially fatal CV thrombotic events: Use lowest effective dose of CAMBIA for shortest possible duration (5.1)
- Serious and potentially fatal GI reactions: Use lowest effective dose of CAMBIA for shortest possible duration; use with caution in patients with prior history of ulcer disease or GI bleeding (5.2)
- Hepatic effects: Range from transaminase elevations to liver failure; discontinue CAMBIA immediately if abnormal liver tests persist or worsen (5.3, 5.13)
- Hypertension: Can occur with NSAID treatment. Monitor blood pressure closely during treatment with CAMBIA (5.4)
- Congestive heart failure and edema: Fluid retention and edema can occur with NSAID treatment; use CAMBIA with caution in patients with fluid retention or heart failure (5.5)
- Renal effects: Long-term administration of NSAIDs can result in renal papillary necrosis and other renal injury; use CAMBIA with caution in patients at risk (e.g., the elderly, those with renal impairment, heart failure, liver impairment, and those taking diuretics or ACE inhibitors) (5.6)
- Anaphylactoid reactions: May occur in patients with the aspirin triad or in patients without prior exposure to CAMBIA; discontinue CAMBIA immediately if an anaphylactoid reaction occurs (5.7)
- Serious skin reactions: Include exfoliative dermatitis, Stevens-Johnson Syndrome, and toxic epidermal necrolysis, which can be fatal; discontinue CAMBIA if rash or other signs of local skin reaction occur (5.8)

6 ADVERSE REACTIONS

Most common adverse reactions (≥1% and >placebo) were nausea and dizziness (6.1)

To report SUSPECTED ADVERSE REACTIONS contact Nautilus Neurosciences, Inc. at 877-874-2440 or FDA at 1-800-FDA-1088 or www.fda.gov/medwatch.

7 DRUG INTERACTIONS

- Aspirin: Concomitant administration with other NSAIDs, including aspirin, is not recommended because of an increased risk of adverse reactions, including GI bleeding (7.1)
- Anticoagulants: Concomitant use of diclofenac and anticoagulants (e.g., warfarin) increases the risk of serious GI bleeding (7.2)

8 USE IN SPECIFIC POPULATIONS

- Pregnancy: Based on animal data, may cause fetal harm. Based on human data, starting at 30 weeks gestation, CAMBIA should be avoided as premature closure of the ductus arteriosus in the fetus may occur (5.9, 8.1)
- Nursing Mothers: Use with caution, as it is not known if diclofenac is excreted in human milk (8.3)
- Hepatic insufficiency: The liver metabolizes almost 100% of diclofenac; there is insufficient information available to support dosing recommendations for CAMBIA in patients with hepatic insufficiency (5.3, 8.6, 12.3)

FULL PRESCRIBING INFORMATION

WARNING: RISK OF SERIOUS CARDIOVASCULAR AND GASTROINTESTINAL EVENTS

Cardiovascular Risk

Non-steroidal anti-inflammatory drugs (NSAIDs) may increase the risk of serious cardiovascular (CV) thrombotic events, myocardial infarction, and stroke, which can be fatal. This risk may increase with duration of use. Patients with cardiovascular disease or risk factors for cardiovascular disease may be at greater risk [see Warnings and Precautions (5.1)].

CAMBIA is contraindicated for the treatment of peri-operative pain in the setting of coronary artery bypass graft (CABG) surgery [see Contraindications (4) and Warnings and Precautions (5.1)].

Gastrointestinal Risk

NSAIDs increase the risk of serious gastrointestinal (GI) adverse events including bleeding, ulceration, and perforation of the stomach or intestines, which can be fatal. These events can occur at any time during use and without warning symptoms. Elderly patients are at greater risk for serious gastrointestinal events [see Warnings and Precautions (5.2)].

1 INDICATIONS AND USAGE

1.1 Acute Treatment of Migraine

CAMBIA™ (Diclofenac Potassium for Oral Solution) is indicated for the acute treatment of migraine attacks with or without aura in adults (18 years of age or older).

1.2 Important Limitations

- CAMBIA is not indicated for the prophylactic therapy of migraine.
- The safety and effectiveness of CAMBIA have not been established for cluster headache, which is present in an older, predominantly male population.

2 DOSAGE AND ADMINISTRATION

2.1 Acute Treatment of Migraine

Administer one packet (50 mg) of CAMBIA™ for the acute treatment of migraine. Empty the contents of one packet into a cup containing 1 to 2 ounces (30 to 60 mL) of water, mix well and drink immediately. Do not use liquids other than water.

Taking CAMBIA with food may cause a reduction in effectiveness compared to taking CAMBIA on an empty stomach [see Clinical Pharmacology (12.3)].

Use the lowest effective dose for the shortest duration consistent with individual patient treatment goals. The safety and effectiveness of a second dose have not been established.

2.2 Interchangeability With Other Formulations of Diclofenac

Different formulations of oral diclofenac (e.g., CAMBIA, diclofenac sodium enteric-coated tablets, diclofenac sodium extended-release tablets, or diclofenac potassium immediate-release tablets) may not be bioequivalent even if the milligram strength is the same. Therefore, it is not possible to convert dosing from any other formulation of diclofenac to CAMBIA.

3 DOSAGE FORMS AND STRENGTHS

CAMBIA is available in individual packets each designed to deliver a 50 mg dose when mixed in water.

4 CONTRAINDICATIONS

- CAMBIA is contraindicated in patients with known hypersensitivity (e.g., anaphylactoid reactions and serious skin reactions) to diclofenac [see Warnings and Precautions (5.7, 5.8)].
- CAMBIA is contraindicated in patients who have experienced asthma, urticaria, or allergic-type reactions after taking aspirin or other NSAIDs. Severe, sometimes fatal, anaphylactic-like reactions to NSAIDs have been reported in such patients [see Warnings and Precautions (5.7, 5.12)].
- CAMBIA is contraindicated for the treatment of peri-operative pain in the setting of coronary artery bypass graft (CABG) surgery [see Warnings and Precautions (5.1)].

5 WARNINGS AND PRECAUTIONS

5.1 Cardiovascular Thrombotic Events

Clinical trials of several COX-2 selective and nonselective NSAIDs of up to three years’ duration have shown an increased risk of serious cardiovascular (CV) thrombotic events, myocardial infarction, and stroke, which can be fatal. All NSAIDs, both COX-2 selective and nonselective, may have a similar risk. Patients with known CV disease or risk factors for CV disease may be at greater risk. To minimize the potential risk for an adverse CV event in patients treated with an NSAID, use the lowest effective dose for the shortest duration possible. Physicians and patients should remain alert for the development of such events, even in the absence of previous CV symptoms. Inform patients about the signs and symptoms of serious CV events and the steps to take if they occur.

There is no consistent evidence that concurrent use of aspirin mitigates the increased risk of serious CV thrombotic events associated with NSAID use. The concurrent use of aspirin and an NSAID increases the risk of serious GI events [see Warnings and Precautions (5.2)].

Two large, controlled, clinical trials of a COX-2 selective NSAID for the treatment of pain in the first 10-14 days following coronary artery bypass graft (CABG) surgery found an increased incidence of myocardial infarction and stroke [see Contraindications (4)].

5.2 Gastrointestinal Effects - Risk of Ulceration, Bleeding, and Perforation

NSAIDs, including CAMBIA, can cause serious gastrointestinal (GI) adverse events such as inflammation, bleeding, ulceration, and perforation of the stomach, small intestine or large intestine, which can be fatal. These serious adverse events can occur at any time, with or without warning symptoms, in patients treated with NSAIDs. Only one in five patients who develop a serious upper GI adverse event on NSAID therapy is symptomatic. Upper GI ulcers, gross bleeding, or perforation caused by NSAIDs occur in approximately 1% of patients treated for 3-6 months, and in about 2%-4% of patients treated for one year. These trends continue with longer duration of use, thus increasing the likelihood of developing a serious GI event at some time during the course of therapy. However, even short-term NSAID therapy is not without risk.

Prescribe NSAIDs, including CAMBIA, with extreme caution in patients with a prior history of ulcer disease or GI bleeding. Patients with a prior history of peptic ulcer disease and/or gastrointestinal bleeding who use NSAIDs have a greater than 10-fold risk for developing a GI bleed than patients with neither of these risk factors. Other factors that increase the risk for GI bleeding in patients treated with NSAIDs include concomitant use of oral corticosteroids or anticoagulants, longer duration of NSAID therapy, smoking, use of alcohol, older age, and poor general health status. Most spontaneous reports of fatal GI events are in elderly or debilitated patients, and therefore special care should be taken in treating this population.

To minimize the potential risk for an adverse GI event in patients treated with an NSAID, use the lowest effective dose for the shortest possible duration. Patients and physicians should remain alert for signs and symptoms of GI ulceration and bleeding during CAMBIA therapy and promptly initiate additional evaluation and treatment if a serious GI adverse event is suspected. This should include discontinuation of the CAMBIA until a serious GI adverse event is ruled out. For high risk patients, alternative therapies that do not include NSAIDs should be considered.

5.3 Hepatic Effects

Elevations of one or more liver tests may occur during therapy with CAMBIA. These laboratory abnormalities may progress, may persist, or may only be transient with continued therapy. Borderline elevations (less than 3 times the upper limit of the normal [ULN] range) or greater elevations of transaminases occurred in about 15% of diclofenac-treated patients. Of the markers of hepatic function, ALT (SGPT) is recommended for the monitoring of liver injury.

In clinical trials, meaningful elevations (i.e., more than 3 times the ULN) of AST (SGOT) occurred in about 2% of approximately 5,700 patients at some time during treatment (ALT was not measured in all studies). In an open-label, controlled trial of 3,700 patients treated for 2–6 months, patients were monitored at 8 weeks and 1,200 patients were monitored again at 24 weeks. Meaningful elevations of ALT and/or AST occurred in about 4% of the 3,700 patients and included marked elevations (>8 times the ULN) in about 1% of the 3,700 patients. In this open-label study, a higher incidence of borderline (less than 3 times the ULN), moderate (3–8 times the ULN), and marked (>8 times the ULN) elevations of ALT or AST was observed in patients receiving diclofenac when compared to other NSAIDs.. Almost all meaningful elevations in transaminases were detected before patients became symptomatic.

Abnormal tests occurred during the first 2 months of therapy with diclofenac in 42 of the 51 patients in all trials who developed marked transaminase elevations. In postmarketing reports, cases of drug-induced hepatotoxicity have been reported in the first month, and in some cases, the first 2 months of NSAID therapy, but can occur at any time during treatment with diclofenac.

Postmarketing surveillance has reported cases of severe hepatic reactions, including liver necrosis, jaundice, fulminant hepatitis with and without jaundice, and liver failure. Some of these reported cases resulted in fatalities or liver transplantation.

Measure transaminases (ALT and AST) periodically in patients receiving long-term therapy with diclofenac because severe hepatotoxicity may develop without a prodrome of distinguishing symptoms. The optimum times for making the first and subsequent transaminase measurements are not known. Based on clinical trial data and postmarketing experiences, transaminases should be monitored within 4 to 8 weeks after initiating treatment with diclofenac. However, severe hepatic reactions can occur at any time during treatment with diclofenac. If abnormal liver tests persist or worsen, if clinical signs and/or symptoms consistent with liver disease develop, or if systemic manifestations occur (e.g., eosinophilia, rash, abdominal pain, diarrhea, dark urine, etc.), discontinue CAMBIA immediately.

To minimize the possibility that hepatic injury will become severe between transaminase measurements, inform patients of the warning signs and symptoms of hepatotoxicity (e.g., nausea, fatigue, lethargy, diarrhea, pruritus, jaundice, right upper quadrant tenderness, and "flu-like" symptoms), and the appropriate action patients should take if these signs and symptoms appear.

To minimize the potential risk for an adverse liver-related event in patients treated with CAMBIA, use the lowest effective dose for the shortest duration possible. Exercise caution when prescribing CAMBIA with concomitant drugs that are known to be potentially hepatotoxic (e.g., acetaminophen, certain antibiotics, antiepileptics). Caution patients to avoid taking nonprescription acetaminophen-containing products while using CAMBIA.

5.4 Hypertension

NSAIDs, including CAMBIA, can lead to new onset or worsening of pre-existing hypertension, either of which may contribute to the increased incidence of CV events. Use NSAIDs, including CAMBIA, with caution in patients with hypertension. Monitor blood pressure closely during the initiation of NSAID treatment and throughout the course of therapy.

Patients taking ACE inhibitors, thiazides, or loop diuretics may have impaired response to these therapies when taking NSAIDs.

5.5 Congestive Heart Failure and Edema

Fluid retention and edema have been observed in some patients taking NSAIDs. Use CAMBIA with caution in patients with fluid retention or heart failure.

5.6 Renal Effects

Use caution when initiating treatment with CAMBIA in patients with considerable dehydration.

Long-term administration of NSAIDs has resulted in renal papillary necrosis and other renal injury. Renal toxicity has also been seen in patients in whom renal prostaglandins have a compensatory role in the maintenance of renal perfusion. In these patients, administration of an NSAID may cause a dose-dependent reduction in prostaglandin formation and, secondarily, in renal blood flow, which may precipitate overt renal decompensation. Patients at greatest risk of this reaction are those with impaired renal function, heart failure, liver dysfunction, those taking diuretics or ACE inhibitors, and the elderly. Discontinuation of NSAID therapy is usually followed by recovery to the pretreatment state.

No information is available from controlled clinical studies regarding the use of CAMBIA in patients with advanced renal disease. Therefore, treatment with CAMBIA is not recommended in patients with advanced renal disease. If CAMBIA therapy must be initiated, close monitoring of the patient's renal function is advisable.

5.7 Anaphylactoid Reactions

As with other NSAIDs, anaphylactoid reactions may occur in patients without known prior exposure to CAMBIA. CAMBIA is contraindicated in patients with the aspirin triad. This symptom complex typically occurs in asthmatic patients who experience rhinitis with or without nasal polyps, or who exhibit severe, potentially fatal bronchospasm after taking aspirin or other NSAIDs. [see Contraindications (4)].

5.8 Serious Skin Reactions

NSAIDs, including CAMBIA, can cause serious skin adverse reactions such as exfoliative dermatitis, Stevens-Johnson Syndrome (SJS), and toxic epidermal necrolysis (TEN), which can be fatal. These serious events may occur without warning. Inform patients about the signs and symptoms of serious skin manifestations and to discontinue CAMBIA at the first appearance of skin rash or any other sign of hypersensitivity.

5.9 Pregnancy

CAMBIA can cause fetal harm when administered to a pregnant woman. Starting at 30 weeks gestation, CAMBIA and other NSAIDs should be avoided by pregnant women as premature closure of the ductus arteriosus in the fetus may occur. If this drug is used during this time period in pregnancy, the patient should be apprised of the potential hazard to a fetus [see Use in Special Populations (8.1)].

5.10 Masking of Inflammation and Fever

The pharmacological activity of NSAIDs in reducing inflammation and possibly fever may diminish the utility of these diagnostic signs in detecting complications of presumed noninfectious, painful conditions.

5.11 Hematologic Effects

Anemia may occur in patients receiving NSAIDs. This may be due to fluid retention, occult or gross GI blood loss, or an incompletely described effect upon erythropoiesis. In patients on long-term therapy with NSAIDs, including CAMBIA, check hemoglobin or hematocrit if they exhibit any signs or symptoms of anemia or blood loss.

NSAIDs inhibit platelet aggregation and have been shown to prolong bleeding time in some patients. Unlike aspirin, the NSAID effect on platelet function is quantitatively less, of shorter duration, and reversible. Carefully monitor patients treated with CAMBIA who may be adversely affected by alterations in platelet function, such as those with coagulation disorders or patients receiving anticoagulants.

5.12 Use in Patients With Pre-existing Asthma

Patients with asthma may have aspirin-sensitive asthma. The use of aspirin in patients with aspirin-sensitive asthma has been associated with severe bronchospasm which can be fatal. Since cross-reactivity, including bronchospasm, between aspirin and other NSAIDs has been reported in such aspirin-sensitive patients, CAMBIA is contraindicated in patients with this form of aspirin sensitivity and should be used with caution in all patients with pre-existing asthma.

5.13 Monitoring

Because serious GI ulcerations and bleeding can occur without warning symptoms, physicians should monitor for signs or symptoms of GI bleeding.

For patients on long-term treatment with NSAIDs, including CAMBIA, periodically perform a CBC and chemistry profile. Discontinue CAMBIA if abnormal liver tests or renal tests persist or worsen.

5.14 Phenylketonurics

CAMBIA contains aspartame equivalent to phenylalanine 25 mg per packet.

6 ADVERSE REACTIONS

The following serious adverse reactions are discussed elsewhere in the labeling:

- Cardiovascular thrombotic events [see Boxed Warning and Warnings and Precautions (5.1)]
- Gastrointestinal effects [see Boxed Warning and Warnings and Precautions (5.2)]
- Hepatic effects [see Warnings and Precautions (5.3)]
- Hypertension [see Warnings and Precautions (5.4)]
- Congestive Heart Failure and Edema [see Warnings and Precautions (5.5)]
- Renal Effects [see Warnings and Precautions (5.6)]
- Anaphylactoid Reactions [see Warnings and Precautions (5.7)]
- Serious Skin Reactions [see Warnings and Precautions (5.8)]

The most common adverse reactions reported with CAMBIA are nausea and dizziness.

The most common adverse events resulting in discontinuation of patients following CAMBIA dosing in controlled clinical trials were urticaria (0.2%) and flushing (0.2%).

6.1 Clinical Studies Experience With CAMBIA

Because clinical trials are conducted under widely varying conditions, adverse reaction rates observed in the clinical trials of a drug cannot be directly compared with rates in the clinical trials of another drug and may not reflect the rates observed in practice.

The safety of a single dose of CAMBIA was evaluated in 2 placebo-controlled trials with a total of 634 migraine patients treated with CAMBIA for a single migraine headache. Following treatment with diclofenac potassium (either CAMBIA or diclofenac potassium immediate-release tablets [as a control]), 5 subjects (0.8%) withdrew from the studies; following placebo exposure, 1 subject (0.2%) withdrew. No withdrawals were due to a serious reaction.

The most common adverse reactions (i.e., that occurred in 1% or more of CAMBIA-treated patients) and more frequent with CAMBIA than with placebo were nausea and dizziness (see Table 1).

Table 1: Treatment-Related Adverse Reactions With Incidence >1% and Greater Than Placebo in Studies 1 and 2 Combined
Disorder Event | CAMBIA N=634 | Placebo N=646
Gastrointestinal Nausea | 3% | 2%
Nervous System Dizziness | 1% | 0.5%

6.2 Adverse Reactions Reported With Diclofenac and Other NSAIDs

In patients taking diclofenac or other NSAIDs, the most frequently reported adverse reactions occurring in approximately 1%-10% of patients are:

GI reactions (including abdominal pain, constipation, diarrhea, dyspepsia, flatulence, gross bleeding/perforation, heartburn, nausea, GI ulcers [gastric/duodenal], and vomiting), abnormal renal function, anemia, dizziness, edema, elevated liver enzymes, headaches, increased bleeding time, pruritus, rashes, and tinnitus.

Additional adverse reactions reported in patients taking NSAIDs include occasionally:

Body as a Whole: Fever, infection, sepsis

Cardiovascular System: Congestive heart failure, hypertension, tachycardia, syncope

Digestive System: Dry mouth, esophagitis, gastric/peptic ulcers, gastritis, gastrointestinal bleeding, glossitis, hematemesis, hepatitis, jaundice

Hemic and Lymphatic System: Ecchymosis, eosinophilia, leukopenia, melena, purpura, rectal bleeding, stomatitis, thrombocytopenia

Metabolic and Nutritional: Weight changes

Nervous System: Anxiety, asthenia, confusion, depression, dream abnormalities, drowsiness, insomnia, malaise, nervousness, paresthesia, somnolence, tremors, vertigo

Respiratory System: Asthma, dyspnea

Skin and Appendages: Alopecia, photosensitivity, sweating increased

Special Senses: Blurred vision

Urogenital System: Cystitis, dysuria, hematuria, interstitial nephritis, oliguria/polyuria, proteinuria, renal failure

Other adverse reactions in patients taking NSAIDs, which occur rarely , are:

Body as a Whole: Anaphylactic reactions, appetite changes, death

Cardiovascular System: Arrhythmia, hypotension, myocardial infarction, palpitations, vasculitis

Digestive System: Colitis, eructation, liver failure, pancreatitis

Hemic and Lymphatic System: Agranulocytosis, hemolytic anemia, aplastic anemia, lymphadenopathy, pancytopenia

Metabolic and Nutritional: Hyperglycemia

Nervous System: Convulsions, coma, hallucinations, meningitis

Respiratory System: Respiratory depression, pneumonia

Skin and Appendages: Angioedema, toxic epidermal necrolysis, erythema multiforme, exfoliative dermatitis, Stevens-Johnson syndrome, urticaria

Special Senses: Conjunctivitis, hearing impairment

7 DRUG INTERACTIONS

7.1 Aspirin

When administered with aspirin, diclofenac potassium’s protein binding is reduced. The clinical significance of this interaction is not known; however, as with other NSAIDs, concomitant administration of CAMBIA and aspirin is not generally recommended because of the potential of increased adverse effects.

7.2 Anticoagulants

The effects of anticoagulants such as warfarin and NSAIDs on GI bleeding are synergistic, such that users of both drugs together have a risk of serious GI bleeding higher than that with use of either drug alone.

7.3 ACE Inhibitors

NSAIDs may diminish the antihypertensive effect of ACE inhibitors. This interaction should be given consideration in patients taking CAMBIA concomitantly with ACE inhibitors.

7.4 Diuretics

Clinical studies, as well as post-marketing observations, have shown that diclofenac potassium can reduce the natriuretic effect of furosemide and thiazides in some patients. This response has been attributed to inhibition of renal prostaglandin synthesis. During concomitant therapy with NSAIDs, observe patients closely for signs of renal failure as well as to assure diuretic efficacy [see Warnings and Precautions (5.6)].

7.5 Lithium

NSAIDs have produced elevations of plasma lithium levels and a reduction in renal lithium clearance. The mean minimum lithium concentration increased 15% and the renal clearance was decreased by approximately 20%. These effects have been attributed to inhibition of renal prostaglandin synthesis by the NSAID. When CAMBIA and lithium are administered concurrently, observe patients carefully for signs of lithium toxicity.

7.6 Methotrexate

NSAIDs have been reported to competitively inhibit methotrexate accumulation in rabbit kidney slices. This indicates that NSAIDs may enhance the toxicity of methotrexate. Use caution when NSAIDs are administered concomitantly with methotrexate.

7.7 Cyclosporine

CAMBIA, like other NSAIDs, may affect renal prostaglandins and increase the toxicity of certain drugs. Therefore, concomitant therapy with CAMBIA may increase cyclosporine's nephrotoxicity. Use caution when CAMBIA is administered concomitantly with cyclosporine.

7.8 Inhibitors of Cytochrome P450 2C9

Diclofenac is metabolized predominantly by Cytochrome P-450 CYP2C9. Co-administration of medications that inhibit CYP2C9 may affect the pharmacokinetics of diclofenac [see Clinical Pharmacology (12.3)].

8 USE IN SPECIFIC POPULATIONS

8.1 Pregnancy

Pregnancy Category C prior to 30 weeks gestation; Category D starting at 30 weeks gestation.

Starting at 30 weeks gestation, CAMBIA, and other NSAIDS, should be avoided by pregnant women as premature closure of the ductus arteriosus in the fetus may occur [see Warnings and Precautions (5.9)]. There are no adequate and well controlled studies in pregnant women.

Prior to 30 weeks gestation, CAMBIA should be used during pregnancy only if the potential benefit justifies the potential risk to the fetus.

Reproductive studies have been performed in mice given diclofenac sodium (up to 20 mg/kg/day, 2 times the recommended human dose [RHD] of 50 mg/day on a body surface area [mg/m^2 basis), and in rats and rabbits given diclofenac sodium (up to 10 mg/kg/day; 2 [rats] and 4 [rabbits] times the RHD on a mg/m^2 basis) and have revealed no evidence of teratogenicity despite the induction of maternal toxicity and fetal toxicity. In rats, maternally toxic doses were associated with dystocia, prolonged gestation, reduced fetal weights and growth, and reduced fetal survival.

8.2 Labor and Delivery

The effects of CAMBIA on labor and delivery in pregnant women are unknown. In rat studies, maternal exposure to NSAIDs, as with other drugs known to inhibit prostaglandin synthesis, increased the incidence of dystocia, delayed parturition, and decreased pup survival.

8.3 Nursing Mothers

It is not known whether this drug is excreted in human milk. Because many drugs are excreted in human milk and because of the potential for serious adverse reactions in nursing infants from CAMBIA, a decision should be made whether to discontinue nursing or to discontinue the drug, taking into account the importance of the drug to the mother.

8.4 Pediatric Use

Safety and effectiveness in pediatric patients have not been established.

8.5 Geriatric Use

Clinical studies of CAMBIA did not include sufficient numbers of subjects aged 65 and over to determine whether they respond differently from younger subjects.

Elderly patients are at increased risk for serious GI adverse events.

Diclofenac is known to be substantially excreted by the kidney, and the risk of adverse reactions to this drug may be greater in patients with impaired renal function. Because elderly patients are more likely to have decreased renal function, care should be taken when using CAMBIA in the elderly.

8.6 Hepatic Impairment

Because hepatic metabolism accounts for almost 100% of diclofenac elimination, patients with hepatic impairment should be considered for treatment with CAMBIA only if the benefits outweigh the risks. There is insufficient information available to support dosing recommendations for CAMBIA in patients with hepatic insufficiency. [see Clinical Pharmacology (12.3)].

8.7 Renal Impairment

No information is available from controlled clinical studies regarding the use of CAMBIA in patients with advanced renal disease. Therefore, treatment with CAMBIA is not recommended in patients with advanced renal disease. If CAMBIA therapy must be initiated, close monitoring of the patient's renal function is advisable.

10 OVERDOSAGE

Symptoms following acute NSAID overdoses are usually limited to lethargy, drowsiness, nausea, vomiting, and epigastric pain, which are generally reversible with supportive care. Gastrointestinal bleeding can occur. Hypertension, acute renal failure, respiratory depression and coma may occur, but are rare. Anaphylactoid reactions have been reported with therapeutic ingestion of NSAIDs, and may occur following an overdose.

Patients should be managed by symptomatic and supportive care following an NSAID overdose. There are no specific antidotes. Emesis and/or activated charcoal (60 to 100 g in adults, 1 to 2 g/kg in children) and/or osmotic cathartic may be indicated in patients seen within 4 hours of ingestion with symptoms or following a large overdose (5 to 10 times the usual dose). Forced diuresis, alkalinization of urine, hemodialysis, or hemoperfusion may not be useful due to high protein binding.

11 DESCRIPTION

CAMBIA (Diclofenac Potassium for Oral Solution) is a benzeneacetic acid derivative NSAID. CAMBIA is available as a buffered soluble powder, designed to be mixed with water prior to oral administration.

CAMBIA is a white to off-white, buffered, flavored powder for oral solution packaged in individual unit dose packets [see How Supplied/Storage and Handling (16)].

The chemical name for diclofenac potassium is 2-[(2,6-dichlorophenyl)amino] benzeneacetic acid monopotassium salt. The molecular weight of diclofenac potassium is 334.25. Its molecular formula is C14H10Cl2NKO2, and it has the following structural formula:

The inactive ingredients in CAMBIA include: aspartame (equivalent to 25 mg phenylalanine), flavoring agents (anise and mint), glycerol behenate, mannitol, potassium bicarbonate, and saccharin sodium.

12 CLINICAL PHARMACOLOGY

12.1 Mechanism of Action

CAMBIA is a non-steroidal anti-inflammatory drug (NSAID). The mechanism of action of CAMBIA, like that of other NSAIDs, is not completely understood but may be related to prostaglandin synthetase inhibition.

12.3 Pharmacokinetics

Absorption: Diclofenac is 100% absorbed after oral administration compared to intravenous administration as measured by urine recovery. However, due to first-pass metabolism, only about 50% of the absorbed dose is systemically available. In fasting volunteers, measurable plasma levels were observed within 5 minutes of dosing with CAMBIA. Peak plasma levels were achieved at approximately 0.25 hour in fasting normal volunteers, with a range of 0.17 to 0.67 hours. High fat food had no significant effect on the extent of diclofenac absorption, but there was a reduction in peak plasma levels of approximately 70% after a high fat meal. Decreased Cmax may be associated to decreased effectiveness.

Distribution: The apparent volume of distribution (V/F) of diclofenac potassium is 1.3 L/kg.

Diclofenac is more than 99% bound to human serum proteins, primarily to albumin. Serum protein binding is constant over the concentration range (0.15-105 µg/mL) achieved with recommended doses.

Metabolism: Five diclofenac metabolites have been identified in human plasma and urine. The metabolites include 4'-hydroxy-, 5-hydroxy-, 3'-hydroxy-, 4',5-dihydroxy- and 3'-hydroxy-4'-methoxy diclofenac. The major diclofenac metabolite, 4’-hydroxydiclofenac, has very weak pharmacologic activity. The formation of 4’-hydroxy diclofenac is primarily mediated by CPY2C9. Both diclofenac and its oxidative metabolites undergo glucuronidation or sulfation followed by biliary excretion. Acylglucuronidation mediated by UGT2B7 and oxidation mediated by CPY2C8 may also play a role in diclofenac metabolism. CYP3A4 is responsible for the formation of minor metabolites, 5-hydroxy and 3’-hydroxy- diclofenac. In patients with renal impairment, peak concentrations of metabolites 4'-hydroxy-and 5- hydroxydiclofenac were approximately 50% and 4% of the parent compound after single oral dosing compared to 27% and 1% in normal healthy subjects.

Excretion: Diclofenac is eliminated through metabolism and subsequent urinary and biliary excretion of the glucuronide and the sulfate conjugates of the metabolites. Little or no free unchanged diclofenac is excreted in the urine. Approximately 65% of the dose is excreted in the urine and approximately 35% in the bile as conjugates of unchanged diclofenac plus metabolites. Because renal elimination is not a significant pathway of elimination for unchanged diclofenac, dosing adjustment in patients with mild to moderate renal dysfunction is not necessary. The terminal half-life of unchanged diclofenac is approximately 2 hours.

Special Populations:

Race: There are no pharmacokinetic differences due to race.

Hepatic Impairment: The liver metabolizes almost 100% of diclofenac; there is insufficient information available to support dosing recommendations for CAMBIA in patients with hepatic insufficiency (5.3, 8.6)

Renal Impairment: In patients with renal impairment (inulin clearance 60-90, 30-60, and <30 mL/min; N=6 in each group), AUC values and elimination rate were comparable to those in healthy subjects.

13 NON-CLINICAL STUDIES

13.1 Carcinogenesis, Mutagenesis, Impairment of Fertility

Long term carcinogenicity studies in rats given diclofenac sodium up to 2 mg/kg/day (less than the recommended human dose [RHD] of 50 mg/day on a body surface area [mg/m^2] basis) have revealed no significant increases in tumor incidence. There was a slight increase in benign mammary fibroadenomas in mid-dose treated (0.5 mg/kg/day or 3 mg/m^2/day) female rats (high-dose females had excessive mortality), but the increase was not significant for this common rat tumor. A 2-year carcinogenicity study conducted in mice employing diclofenac sodium at doses up to 0.3 mg/kg/day (less than the RHD on a mg/m^2 basis) in males and 1 m/kg/day (less than the RHD on a mg/m^2 basis) in females did not reveal any oncogenic potential.

Diclofenac sodium was not genotoxic in in vitro (reverse mutation in bacteria [Ames], mouse lymphoma tk) or in in vivo (including dominant lethal and male germinal epithelial chromosomal aberration in Chinese hamster) assays.

Diclofenac sodium administered to male and female rats at 4 mg/kg/day (less than the RHD on a mg/m^2 basis) did not affect fertility.

14 CLINICAL STUDIES

The efficacy of CAMBIA in the acute treatment of migraine headache was demonstrated in two randomized, double-blind, placebo-controlled trials.

Patients enrolled in these two trials were predominantly female (85%) and white (86%), with a mean age of 40 years (range: 18 to 65). Patients were instructed to treat a migraine of moderate to severe pain with 1 dose of study medication. Patients evaluated their headache pain 2 hours later. Associated symptoms of nausea, photophobia, and phonophobia were also evaluated. In addition, the proportion of patients who were “sustained pain free”, defined as a reduction in headache severity from moderate or severe pain to no pain at 2 hours post-dose without a return of mild, moderate, or severe pain and no use of rescue medication for 24 hours post-dose, was also evaluated. In these studies, the percentage of patients achieving pain freedom 2 hours after treatment and sustained pain freedom from 2 to 24 hours post-dose was significantly greater in patients who received CAMBIA compared with those who received placebo (see Table 2). The percentage of patients achieving pain relief 2 hours after treatment (defined as a reduction in headache severity from moderate or severe pain to mild or no pain) was also significantly greater in patients who received CAMBIA compared with those who received placebo (see Table 2).

Table 2: Percentage of Patients With 2-Hour Pain Freedom, Sustained Pain Freedom 2-24 Hours, and 2-Hour Pain Relief Following Treatment
Study 1 | CAMBIA (n=265) | Placebo (n=257)
2-Hour Pain Free | 24% | 13%
2-24h Sustained Pain Free | 22% | 10%
2-Hour Pain Relief | 48% | 27%
Study 2 | CAMBIA (n=343) | Placebo (n=347)
2-Hour Pain Free | 25% | 10%
2-24h Sustained Pain Free | 19% | 7%
2-Hour Pain Relief | 65% | 41%

The estimated probability of achieving migraine headache pain freedom within 2 hours following treatment with CAMBIA is shown in Figure 1.

Figure 1. Percentage of Patients With Initial Headache Pain Freedom Within 2 Hours

There was a decreased incidence of nausea, photophobia and phonophobia following administration of CAMBIA, compared to placebo. The efficacy and safety of CAMBIA was unaffected by age or gender of the patient.

16 HOW SUPPLIED/STORAGE AND HANDLING

CAMBIA™ 50 mg (Diclofenac Potassium for Oral Solution) is supplied as one or more sets of three perforated co-joined individual dose packets. Each individual packet is designed to deliver a dose of 50 mg diclofenac potassium when mixed in water.

CAMBIA is a white to off-white, buffered, flavored powder for oral solution packaged in individual unit dose packets.

Individual CAMBIA™ Packets - NDC 50192-113-01

Boxes of nine (9) CAMBIA™ Packets - NDC 50192-113-09

Store at 25°C (77°F) Excursions permitted from 15°C-30°C (59°F-86°F). [See USP Controlled Room Temperature]

Manufactured by:
MIPHARM S.p.A.
Via Bernardo Quaranta, 12
20141 Milan, Italy

Manufactured for:
Nautilus Neurosciences, Inc.
135 Rte. 202/206
Bedminster, NJ 08921
United States of America

Manufactured and Distributed Under License from APR Applied Pharma Research SA, Balerna Switzerland

17 PATIENT COUNSELING INFORMATION

Inform patients of the availability of a Medication Guide for NSAIDs that accompanies each prescription dispensed, and instruct them to read the Medication Guide prior to using CAMBIA [see Medication Guide (17.9)].

17.1 Cardiovascular Effects

CAMBIA, like other NSAIDS, may cause serious CV events, such as MI or stroke, which may result in hospitalization and even death. Although serious CV events can occur without warning symptoms, advise patients to be alert for the signs and symptoms of chest pain, shortness of breath, weakness, slurring of speech, and to ask for medical advice when observing any indicative sign or symptoms. Inform patients of the importance of this follow-up [see Warnings and Precautions (5.1)].

17.2 Gastrointestinal Effects

CAMBIA, like other NSAIDS, can cause GI discomfort and more serious GI adverse events such as ulcers and bleeding, which may result in hospitalization and even death. Although serious GI tract ulcerations and bleeding can occur without warning symptoms, advise patients to be alert for the signs and symptoms of ulcerations and bleeding, and to ask for medical advice when observing any indicative sign or symptoms including epigastric pain, dyspepsia, melena, and hematemesis. Inform patients of the importance of this follow-up [see Warnings and Precautions (5.2)].

17.3 Hepatotoxicity

Inform patients of the warning signs and symptoms of hepatotoxicity (e.g., nausea, fatigue, lethargy, pruritus, jaundice, right upper quadrant tenderness, and “flulike” symptoms). Instruct patients to stop therapy with CAMBIA and seek immediate medical therapy if any of these occur [see Warnings and Precautions (5.3)].

17.4 Weight Gain and Edema

Advise patients to promptly report to their physicians signs or symptoms of unexplained weight gain or edema during treatment with CAMBIA [see Warnings and Precautions (5.5)].

17.5 Anaphylactoid Reactions

Inform patients of the signs of an anaphylactoid reaction (e.g., difficulty breathing, swelling of the face or throat). Instruct patients to seek immediate emergency help if these occur [see Warnings and Precautions (5.7)].

17.6 Adverse Skin Reactions

CAMBIA, like other NSAIDS, can cause serious skin reactions such as exfoliative dermatitis, Stevens-Johnson syndrome (SJS), and toxic epidermal necrosis (TEN), which may result in hospitalizations and even death. Although serious skin reactions may occur without warning, advise patients to be alert for the signs and symptoms of skin rash and blisters, fever, or other signs of hypersensitivity such as itching, and to ask for medical advice when observing any indicative signs or symptoms. Advise patients to stop CAMBIA immediately if they develop any type of rash and to contact their physicians as soon as possible [see Warnings and Precautions (5.8)].

17.7 Effects During Pregnancy

Starting at 30 weeks gestation, CAMBIA and other NSAIDs should be avoided by pregnant women as premature closure of the ductus arteriosus in the fetus may occur [see Use in Specific Populations (8.1)].

17.8 Phenylketonurics

CAMBIA packets contain aspartame equivalent to phenylalanine 25 mg per packet.

17.9 FDA-Approved Medication Guide

Upon dispensing to a patient please ensure the patient receives the attached Medication Guide.

MEDGUIDE

MEDICATION GUIDE

CAMBIA (Cam-bē-ə or Cam-bē-a)
(diclofenac potassium for oral solution)

Read the Patient Information that comes with CAMBIA before you start taking it and each time you get a refill. There may be new information. This leaflet does not take the place of talking with your doctor about your medical condition or your treatment.

What is the most important information I should know about CAMBIA?

CAMBIA, which contains diclofenac, (a non-steroidal anti-inflammatory drug or NSAID), may increase your chance of a heart attack or stroke that can lead to death. This chance is higher:

- with longer use of NSAID medicines
- in people who have heart disease

NSAID medicines, such as CAMBIA, should never be used right before or after a heart surgery called a “coronary artery bypass graft” (CABG).

NSAID medicines, such as CAMBIA, can cause ulcers and bleeding in your stomach and intestines at any time during treatment.

Ulcers and bleeding:

- can happen without warning symptoms
- may cause death

The chance of a person getting an ulcer or bleeding increases with:

- the use of medicines called steroid hormones (corticosteroids) and blood thinners (anticoagulants)
- longer or regular use
- smoking
- drinking alcohol
- older age
- having poor health

CAMBIA should only be used:

- exactly as prescribed
- at the lowest dose possible for your treatment
- for the shortest time needed

What is CAMBIA?

CAMBIA is a prescription medicine used to treat migraine attacks in adults. It does not prevent or lessen the number of migraines you have, and it is not for other types of headaches. CAMBIA contains diclofenac potassium (a Non-Steroidal Anti-Inflammatory Drug or NSAID).

How should I take CAMBIA?

Take CAMBIA exactly as your healthcare provider tells you to take it.

Take 1 dose of CAMBIA to treat your migraine headache:

- remove one single dose packet from a set of three packets
- open packet only when you are ready to use it
- empty contents of packet into 1 to 2 ounces (2 to 4 tablespoons) of water
- mix well and drink the water and powder mixture
- throw away empty packet in a safe place and out of the reach of children
- taking CAMBIA with food may cause a reduction in effectiveness compared to taking CAMBIA on an empty stomach
- do not take more CAMBIA than directed by your healthcare provider. In case of overdose, get medical help or contact a Poison Control Center right away

Who should not take CAMBIA?

Do not take CAMBIA:

- right before or after heart bypass surgery. See “What is the most important information I should know about CAMBIA?”
- if you have or have had an asthma attack, hives, or other allergic reaction with aspirin, diclofenac, or any other NSAID medicine

Before you take CAMBIA, tell your healthcare provider about all your medical conditions, including if you:

- have a history of stomach ulcer or bleeding in your stomach or intestines
- have kidney or liver problems
- have any allergies to any medicines
- have chest pain, shortness of breath, irregular heartbeats
- are pregnant, think you might be pregnant, or are trying to become pregnant. CAMBIA should not be used by pregnant women, especially during the last 3 months of pregnancy unless directed by your healthcare provider to do so. CAMBIA may cause problems in your unborn child or complications during your delivery
- are breastfeeding or plan to breastfeed. It is not known if CAMBIA passes into your breast milk. You and your doctor should decide if you will take CAMBIA or breastfeed. You should not do both
- have a headache that is different from your usual migraine

Tell your doctor about all the medicines you take, including prescription and non-prescription medicines, vitamins, and herbal supplements.

CAMBIA and other medicines may affect each other, causing side effects. CAMBIA may affect the way other medicines work, and other medicines may affect how CAMBIA works.

Especially tell your doctor if you take:

- aspirin
- any anticoagulant medicines (warfarin, Coumadin, Jantoven)

Know the medicines you take. Keep a list of your medicines and show it to your doctor and pharmacist when you get a new medicine.

What are the possible side effects of CAMBIA?

Serious side effects include:

- heart attack
- stroke
- high blood pressure
- heart failure from body swelling (fluid retention)
- kidney problems including kidney failure
- bleeding and ulcers in the stomach and intestine
- low red blood cells (anemia)
- life-threatening skin reactions
- life-threatening allergic reactions
- liver problems including life-threatening liver failure
- asthma attacks in people who have asthma

Get emergency help right away if you have any of the following symptoms of heart attack or stroke:

- shortness of breath or trouble breathing
- chest pain
- swelling of your face or throat
- weakness in one part or one side of your body
- slurred speech

Common side effects include:

- nausea
- dizziness

Stop CAMBIA and call your healthcare provider right away if you have any of the following symptoms:

- nausea that seems out of proportion to your migraine
- stomach pain
- sudden or severe pain in your belly
- vomit blood
- blood in your bowel movement or it is black and sticky like tar
- itching
- skin rash or blisters with fever
- yellow skin or eyes
- swelling of your arms and legs, hands and feet
- unusual weight gain
- more tired or weaker than usual
- flu-like symptoms

Tell your healthcare provider if you have any side effects that bother you or do not go away.

These are not all the side effects with NSAID medicines. Talk to your healthcare provider or pharmacist for more information about NSAID medicines.

Call your healthcare provider for medical advice about side effects. You may report side effects to FDA at 1-800-FDA-1088.

How should I store CAMBIA?

- store CAMBIA in a dry place at room temperature between 59° to 86°F (15° to 30°C)
- keep CAMBIA and all medicines out of reach of children

General information about CAMBIA

- medicines are sometimes prescribed for purposes other than those listed in a Medication Guide. Do not use CAMBIA for a condition for which it was not prescribed
- do not give CAMBIA to other people, even if they have the same problem you have. It may harm them
- this Medication Guide contains the most important information about CAMBIA. If you would like more information, talk with your healthcare provider. You can ask your healthcare provider for information written for healthcare professionals
- for more information call Nautilus Neurosciences, Inc at 877-874-2440 (weekdays 9 AM to 5 PM EST) or through our website at www.nautilusneurosciences.com

What are the ingredients in CAMBIA?

Active ingredients: diclofenac potassium

Inactive ingredients: aspartame (equivalent to 25 mg phenylalanine), flavoring agents (anise and mint), glyceryl behenate, mannitol, potassium bicarbonate, and saccharin sodium

Rx only
Issued June 2009
Nautilus Neurosciences, Inc.
Bedminster, NJ 07921
United States of America

This Medication Guide has been approved by the U.S. Food and Drug Administration.

PRINCIPAL DISPLAY PANEL

CAMBIATM
Diclofenac Potassium for Oral Solution
50 mg
Rx Only
WARNING: Phenylketonurics: Product contains Aspartame,
equivalent to 25 mg phenylalanine
KEEP OUT OF THE REACH OF CHILDREN.
Contains three (3) total packets.
NAUTILUS
NEROSCIENCES